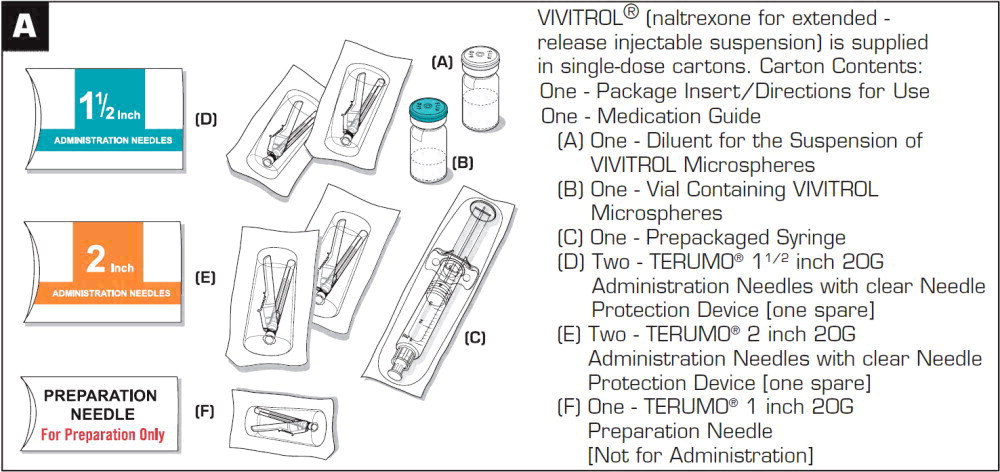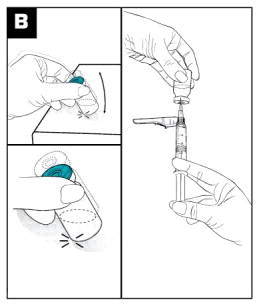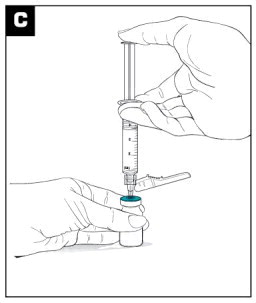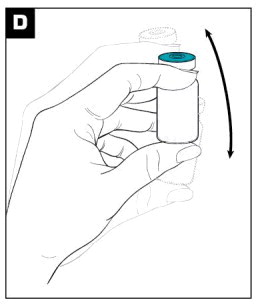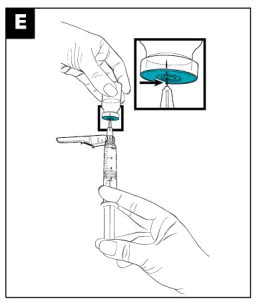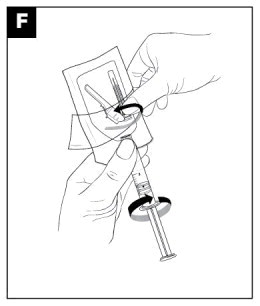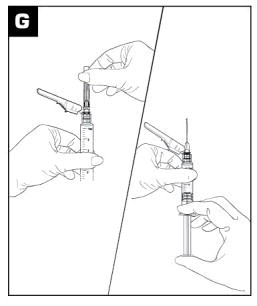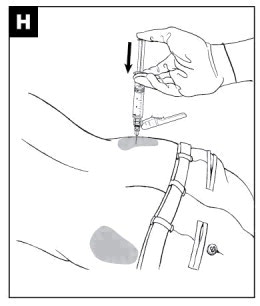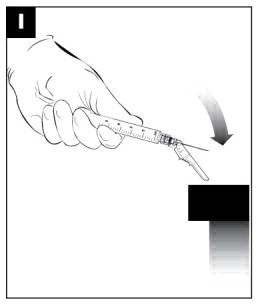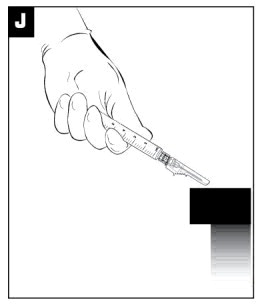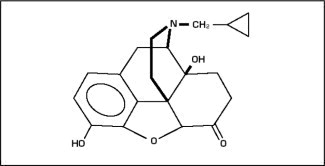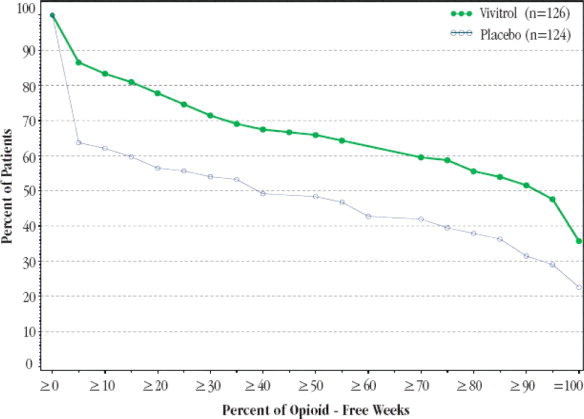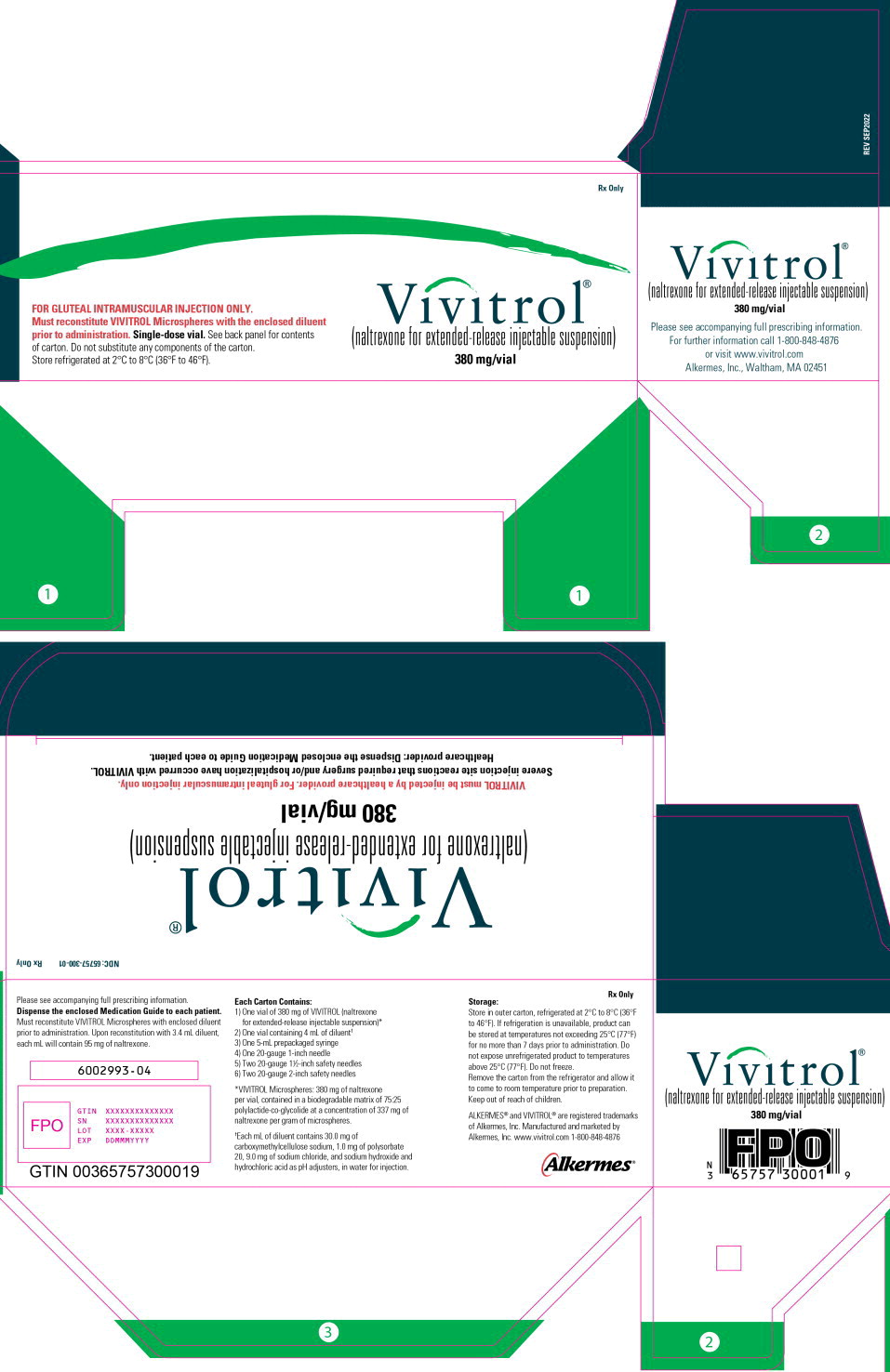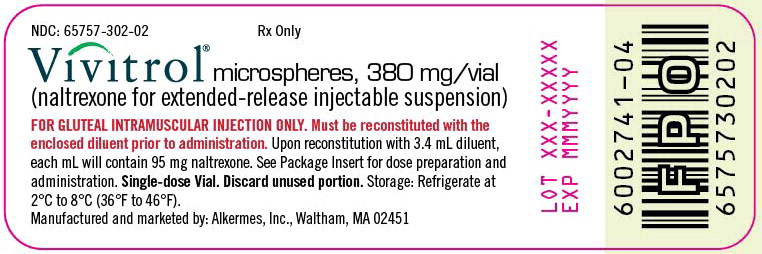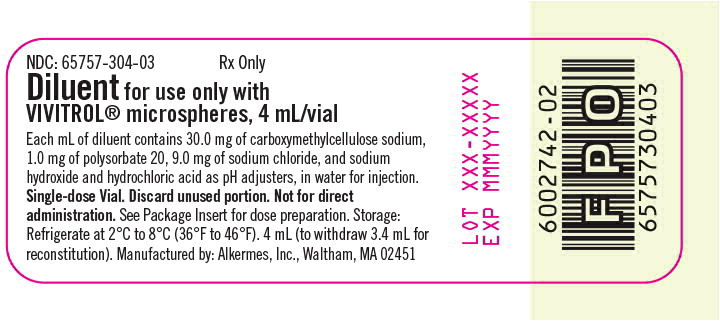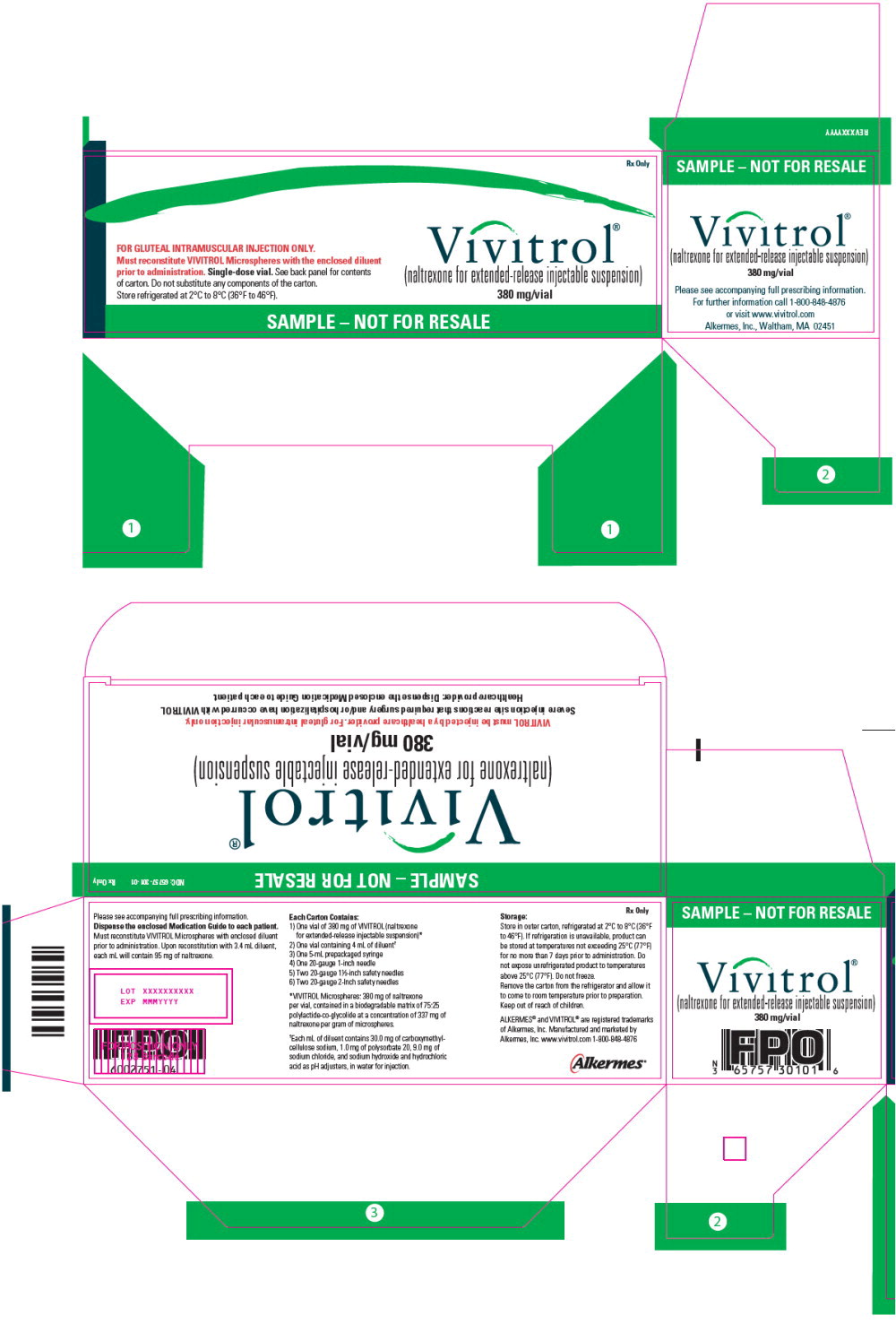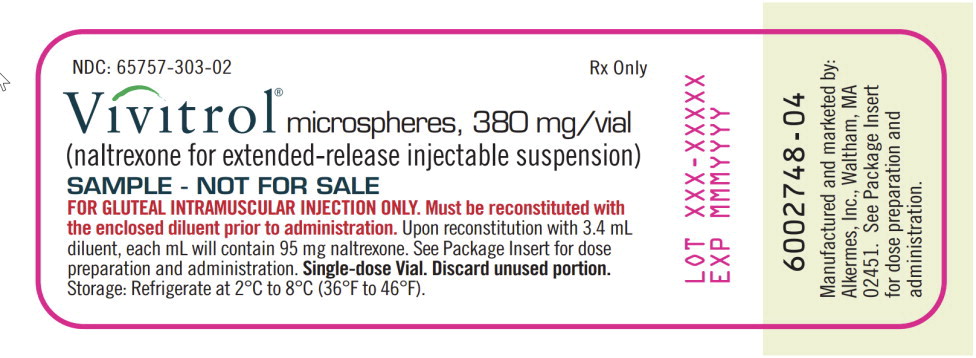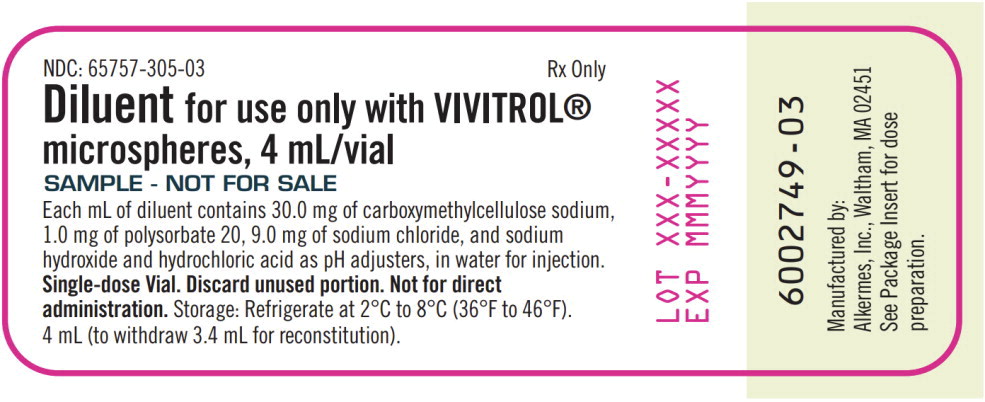 DRUG LABEL: VIVITROL
NDC: 65757-300 | Form: KIT | Route: INTRAMUSCULAR
Manufacturer: Alkermes, Inc.
Category: prescription | Type: HUMAN PRESCRIPTION DRUG LABEL
Date: 20251223

ACTIVE INGREDIENTS: naltrexone 380 mg/4 mL
INACTIVE INGREDIENTS: carboxymethylcellulose sodium, unspecified form 30.0 mg/1 mL; polysorbate 20 1.0 mg/1 mL; sodium chloride 9.0 mg/1 mL; water; sodium hydroxide; hydrochloric acid

HIGHLIGHTS OF PRESCRIBING INFORMATION

These highlights do not include all the information needed to use VIVITROL® safely and effectively. See full prescribing information for VIVITROL.
VIVITROL (naltrexone for extended-release injectable suspension), for intramuscular use
Initial U.S. Approval: 1984

RECENT MAJOR CHANGES

Dosage and Administration (2.2) | 12/2025
Warnings and Precautions (5.1) | 12/2025

1 INDICATIONS AND USAGE

- VIVITROL contains naltrexone, an opioid antagonist, and is indicated for the treatment of alcohol dependence in patients who are able to abstain from alcohol in an outpatient setting prior to initiation of treatment with VIVITROL. Patients should not be actively drinking at the time of initial VIVITROL administration (1.1).
- VIVITROL is indicated for the prevention of relapse to opioid dependence, following opioid detoxification (1.2).
- VIVITROL should be part of a comprehensive management program that includes psychosocial support (1).

2 DOSAGE AND ADMINISTRATION

- VIVITROL must be prepared and administered by a healthcare provider (2.1, 2.6).
- Prior to initiating VIVITROL, an opioid-free duration of a minimum of 7–10 days is recommended for patients, to avoid precipitation of opioid withdrawal that may be severe enough to require hospitalization (2.1).
- The recommended dose of VIVITROL is 380 mg delivered intramuscularly (deep) as a gluteal injection, every 4 weeks or once a month, alternating buttocks for each subsequent injection, using the carton components provided (2.1).
- VIVITROL must ONLY be administered as a deep intramuscular gluteal injection (2.1).
- See Full Prescribing Information for complete Directions for Use (2.6).

3 DOSAGE FORMS AND STRENGTHS

VIVITROL is an injectable suspension containing 380 mg of naltrexone in a microsphere formulation in a single-dose vial (3).

4 CONTRAINDICATIONS

VIVITROL is contraindicated in:

- Patients receiving opioid analgesics (4).
- Patients with current physiologic opioid dependence (4).
- Patients in acute opioid withdrawal (4).
- Any individual who has failed the naloxone challenge test or has a positive urine screen for opioids (4).
- Patients who have previously exhibited hypersensitivity to naltrexone, polylactide-co-glycolide (PLG), carboxymethylcellulose, or any other components of the diluent (4).

5 WARNINGS AND PRECAUTIONS

- Vulnerability to Opioid Overdose: Following VIVITROL treatment, opioid tolerance is reduced from pretreatment baseline and patients are vulnerable to potentially fatal overdose at the end of a dosing interval, after missing a dose, or after discontinuing VIVITROL treatment. Attempts to overcome blockade may also lead to fatal overdose. Strongly consider recommending or prescribing an opioid reversal agent (e.g., naloxone, nalmefene) for the emergency treatment of opioid overdose (5.1).
- Injection Site Reactions: VIVITROL must be prepared and administered by a healthcare provider. In some cases, injection site reactions may be very severe. Some cases of injection site reactions required surgical intervention (5.2).
- Precipitation of Opioid Withdrawal: Opioid-dependent and opioid-using patients, including those being treated for alcohol dependence, should be opioid-free before starting VIVITROL treatment, and should notify healthcare providers of any recent opioid use. An opioid-free duration of a minimum of 7-10 days is recommended for patients to avoid precipitation of opioid withdrawal that may be severe enough to require hospitalization (5.3).
- Hepatotoxicity: Cases of hepatitis and clinically significant liver dysfunction were observed in association with VIVITROL treatment during the clinical development program and in the postmarketing period. Discontinue use of VIVITROL in the event of symptoms or signs of acute hepatitis (5.4).
- Depression and Suicidality: Monitor patients for the development of depression or suicidal thinking (5.5).
- When Reversal of VIVITROL Blockade Is Required for Pain Management: In an emergency situation in patients receiving VIVITROL, suggestions for pain management include regional analgesia or use of non-opioid analgesics (5.6).
- Eosinophilic Pneumonia: Patients who develop dyspnea and hypoxemia should seek medical attention immediately. Consider the possibility of eosinophilic pneumonia in patients who do not respond to antibiotics (5.7).
- Hypersensitivity Reactions Including Anaphylaxis: Cases of urticaria, angioedema, and anaphylaxis have been observed with the use of VIVITROL (5.8).

6 ADVERSE REACTIONS

The adverse events seen most frequently in association with VIVITROL therapy for alcohol dependence (i.e, those occurring in ≥5% and at least twice as frequently with VIVITROL than placebo) include nausea, vomiting, injection site reactions (including induration, pruritus, nodules and swelling), muscle cramps, dizziness or syncope, somnolence or sedation, anorexia, decreased appetite or other appetite disorders (6).

The adverse events seen most frequently in association with VIVITROL therapy in opioid-dependent patients (i.e., those occurring in ≥2% of patients treated with VIVITROL and at least twice as frequently with VIVITROL than placebo) were hepatic enzyme abnormalities, injection site pain, nasopharyngitis, insomnia, and toothache (6).

To report SUSPECTED ADVERSE REACTIONS, contact Alkermes, Inc. at 1-800-VIVITROL (1-800-848-4876) and/or email: usmedinfo@alkermes.com or FDA at 1-800-FDA-1088 or www.fda.gov/medwatch.

7 DRUG INTERACTIONS

Naltrexone antagonizes the effects of opioid-containing medicines, such as cough and cold remedies, antidiarrheal preparations, and opioid analgesics (7).

8 USE IN SPECIFIC POPULATIONS

- Caution is recommended in administering VIVITROL to patients with moderate to severe renal impairment (8.6).
- VIVITROL pharmacokinetics have not been evaluated in subjects with severe hepatic impairment (8.7).

FULL PRESCRIBING INFORMATION

1 INDICATIONS AND USAGE

Treatment with VIVITROL should be part of a comprehensive management program that includes psychosocial support.

1.1 Alcohol Dependence

VIVITROL is indicated for the treatment of alcohol dependence in patients who are able to abstain from alcohol in an outpatient setting prior to initiation of treatment with VIVITROL. Patients should not be actively drinking at the time of initial VIVITROL administration.

1.2 Opioid Dependence

VIVITROL is indicated for the prevention of relapse to opioid dependence, following opioid detoxification.

2 DOSAGE AND ADMINISTRATION

2.1 Important Dosage and Administration Information

VIVITROL must be prepared and administered by a healthcare provider.

VIVITROL must ONLY be administered as a deep intramuscular gluteal injection.

Parenteral products should be visually inspected for particulate matter and discoloration prior to administration whenever solution and container permit. A properly mixed suspension will be milky white, will not contain clumps, and will move freely down the wall of the vial [see Dosage and Administration (2.6)].

Prior to initiating VIVITROL, an opioid-free duration of a minimum of 7–10 days is recommended for patients, to avoid precipitation of opioid withdrawal that may be severe enough to require hospitalization [see Warnings and Precautions (5.3)].

The recommended dose of VIVITROL is 380 mg delivered intramuscularly (deep) as a gluteal injection every 4 weeks or once a month, alternating buttocks for each subsequent injection, using the carton components provided [see How Supplied/Storage and Handling (16)]. The needles provided in the carton are customized needles. VIVITROL must not be injected using any other needle. The needle lengths (either 1 1/2 or 2 inches) may not be adequate in every patient because of body habitus. Body habitus should be assessed prior to each injection for each patient to assure that needle length is adequate for intramuscular administration. For patients with a larger amount of subcutaneous tissue overlying the gluteal muscle, the administering healthcare provider may utilize the supplied 2-inch needle with needle protection device to help ensure that the injectate reaches the intramuscular mass. For very lean patients, the 1 1/2-inch needle may be appropriate to prevent the needle contacting the periosteum. Either needle may be used for patients with average body habitus. Healthcare providers should ensure that the VIVITROL injection is given correctly, and should consider alternate treatment for those patients whose body habitus precludes an intramuscular gluteal injection with one of the provided needles.

If a patient misses a dose, he/she should be instructed to receive the next dose as soon as possible.

Pretreatment with oral naltrexone is not required before using VIVITROL.

2.2 Patient Access to an Opioid Reversal Agent for the Emergency Treatment of Opioid Overdose

At the initial VIVITROL injection and with each subsequent injection, inform patients and caregivers about opioid overdose reversal agents (e.g., naloxone, nalmefene) and discuss the importance of having access to an opioid overdose reversal agent. Because patients being treated for opioid use disorder have the potential for relapse, putting them at risk for opioid overdose after VIVITROL treatment is discontinued, at the end of the VIVITROL dosing interval (i.e., near the end of the month that VIVITROL was administered), or after a dose of VIVITROL is missed, strongly consider recommending or prescribing an overdose reversal agent for the emergency treatment of opioid overdose [see Warnings and Precautions (5.1)].

Discuss the options for obtaining an opioid overdose reversal agent (e.g., prescription, over-the-counter, or as part of a community-based program [see Warning and Precautions (5.1)].

There are important differences among the opioid overdose reversal agents, such as route of administration, product strength, approved patient age range, and pharmacokinetics. Be familiar with these differences, as outlined in the approved labeling for those products, prior to recommending or prescribing such an agent.

2.3 Reinitiation of Treatment in Patients Previously Discontinued

There are no data to specifically address reinitiation of treatment. Patients reinitiating treatment with VIVITROL should be opioid-free at the time of dose administration [see Indications and Usage (1), Contraindications (4), and Warnings and Precautions (5.3)].

2.4 Switching From Oral Naltrexone

There are no systematically collected data that specifically address the switch from oral naltrexone to VIVITROL.

2.5 Switching from Buprenorphine, Buprenorphine/Naloxone, or Methadone

There are no systematically collected data that specifically address the switch from buprenorphine or methadone to VIVITROL; however, review of postmarketing case reports have indicated that some patients may experience severe manifestations of precipitated withdrawal when being switched from opioid agonist therapy to opioid antagonist therapy [see Warnings and Precautions (5.3)]. Patients transitioning from buprenorphine or methadone may be vulnerable to precipitation of withdrawal symptoms for as long as 2 weeks. Healthcare providers should be prepared to manage withdrawal symptomatically with non-opioid medications.

2.6 Directions for Use

VIVITROL must be prepared and administered by a healthcare provider.

VIVITROL must ONLY be administered as a deep intramuscular gluteal injection.

To ensure proper dosing, it is important that you follow the preparation and administration instructions outlined in this document.

VIVITROL must be suspended only in the diluent supplied in the carton and must be administered only with one of the administration needles supplied in the carton. The microspheres, diluent, preparation needle, and an administration needle with needle protection device are required for preparation and administration. Two thin-walled 1 1/2-inch needles with needle protection device and two 2-inch thin-walled needles with needle protection device have been provided to accommodate varying patient body habitus. For patients with a larger amount of subcutaneous tissue overlying the gluteal muscle, the administering healthcare provider may utilize the supplied 2-inch needle with needle protection device to help ensure that the injectate reaches the intramuscular mass. For very lean patients, the 1 1/2-inch needle may be appropriate to prevent the needle contacting the periosteum. Either needle may be used for patients with average body habitus. A spare administration needle of each size is provided in case of clogging [see How Supplied/Storage and Handling (16)]. Do not substitute any other components for the components of the carton.

Prior to preparation, allow drug to reach room temperature (approximately 45 minutes).

Parenteral products should be visually inspected for particulate matter and discoloration prior to administration whenever solution and container permit. A properly mixed suspension will be milky white, will not contain clumps, and will move freely down the wall of the vial [see Directions for Use, illustration below].

Keep out of reach of children.

Prepare and administer the VIVITROL suspension using aseptic technique.

WARNING: To reduce the risk of a needlestick:

- Do not intentionally disengage the needle protection device.
- Discard bent or damaged needle into a sharps container and use the spare needle provided. Do not attempt to straighten the needle or engage needle protection device if the needle is bent or damaged.
- Do not mishandle the needle protection device in a way that could lead to protrusion of the needle.
- Do not use free hand to press sheath over needle.

THE CARTON SHOULD NOT BE EXPOSED TO TEMPERATURES EXCEEDING 25 °C (77 °F).

The entire carton should be stored in the refrigerator (2 °C to 8 °C, 36 °F to 46 °F). Unrefrigerated, VIVITROL microspheres can be stored at temperatures not exceeding 25 °C (77 °F) for no more than 7 days prior to administration. Do not expose unrefrigerated product to temperatures above 25 °C (77 °F). VIVITROL should not be frozen.

Parenteral products should be visually inspected for particulate matter and discoloration prior to administration.

1. Remove the carton from refrigeration. Prior to preparation, allow drug to reach room temperature (approximately 45 minutes).
2. To ease mixing, firmly tap the VIVITROL microspheres vial on a hard surface, ensuring the powder moves freely. (see Figure B)
3. Remove flip-off caps from both vials. DO NOT USE IF FLIP-OFF CAPS ARE BROKEN OR MISSING.
4. Wipe the vial tops with an alcohol swab.
5. Place the 1-inch preparation needle on the syringe and withdraw 3.4 mL of the diluent from the diluent vial. Some diluent will remain in the diluent vial. (see Figure B)

Inject the 3.4 mL of diluent into the VIVITROL microsphere vial. (see Figure C)

Mix the powder and diluent by vigorously shaking the vial for approximately 1 minute. (see Figure D)
Ensure that the dose is thoroughly suspended prior to proceeding to Step E.
A PROPERLY MIXED SUSPENSION WILL BE MILKY WHITE, WILL NOT CONTAIN CLUMPS, AND WILL MOVE FREELY DOWN THE WALLS OF THE VIAL.

1. Immediately after suspension, withdraw 4.2 mL of the suspension into the syringe using the same preparation needle. (see Figure E)
2. Select the appropriate needle for a deep intramuscular injection based on patient's body habitus:
  1. 1 1/2-inch TERUMO® Needle
  2. 2-inch TERUMO® Needle

1. Remove the preparation needle and replace with appropriately selected administration needle for immediate use.
2. Peel the blister pouch of the selected administration needle open halfway. Grip the base of the needle, not the safety sheath. Attach the luer connection to the syringe with an easy clockwise twisting motion. (see Figure F)
3. Seat the needle firmly on the needle protection device with a push and clockwise twist.

1. Move the safety sheath away from the needle and toward the syringe barrel. Pull the sheath away from the needle -do not twist the sheath because it could result in loosening the needle.
2. Prior to injecting, tap the syringe to release any air bubbles, then push gently on the plunger until 4 mL of the suspension remains in the syringe. (see Figure G)

THE SUSPENSION IS NOW READY FOR IMMEDIATE ADMINISTRATION

1. Using a circular motion, clean the injection site with the alcohol swab. Let the site dry before injecting. Do not touch the site again before giving injections.
2. Administer the suspension by deep intramuscular (IM) injection into a gluteal muscle, alternating buttocks per monthly injection. Remember to aspirate for blood before injection. (see Figure H)
3. If blood aspirates or the needle clogs, do not inject. Change to the spare needle provided in the carton and administer into an adjacent site in the same gluteal region, again aspirating for blood before injection.
4. Inject the suspension in a smooth and continuous motion.

VIVITROL must ONLY be administered as a deep intramuscular gluteal injection.

After the injection is administered, cover the needle by pressing the needle protection device against a flat surface using a one-handed technique to activate the safety mechanism away from self and others. (see Figure I)

Visually confirm needle is fully engaged into the needle protection device. (see Figure J)
DISPOSE OF USED AND UNUSED ITEMS IN PROPER WASTE CONTAINERS.

3 DOSAGE FORMS AND STRENGTHS

VIVITROL is an off-white to light tan powder for injectable suspension in a 5 mL single-dose vial.

VIVITROL contains 380 mg of naltrexone in a microsphere formulation per vial (337 mg of naltrexone per gram of microspheres).

4 CONTRAINDICATIONS

VIVITROL is contraindicated in:

- Patients receiving opioid analgesics [see Warnings and Precautions (5.3)].
- Patients with current physiologic opioid dependence [see Warnings and Precautions (5.3)].
- Patients in acute opioid withdrawal [see Warnings and Precautions (5.3)].
- Any individual who has failed the naloxone challenge test or has a positive urine screen for opioids [see Warnings and Precautions (5.3)].
- Patients who have previously exhibited hypersensitivity to naltrexone, PLG, carboxymethylcellulose, or any other components of the diluent [see Warnings and Precautions (5.8)].

5 WARNINGS AND PRECAUTIONS

5.1 Vulnerability to Opioid Overdose

After opioid detoxification, patients are likely to have reduced tolerance to opioids. VIVITROL blocks the effects of exogenous opioids for approximately 28 days after administration. However, as the blockade wanes and eventually dissipates completely, patients who have been treated with VIVITROL may respond to lower doses of opioids than previously used, just as they would have shortly after completing detoxification. This could result in potentially life-threatening opioid intoxication (respiratory compromise or arrest, circulatory collapse, etc.) if the patient uses previously tolerated doses of opioids. Cases of opioid overdose with fatal outcomes have been reported in patients who used opioids at the end of a dosing interval, after missing a scheduled dose, or after discontinuing treatment.

Patients should be alerted that they may be more sensitive to opioids, even at lower doses, after VIVITROL treatment is discontinued, especially at the end of a dosing interval (i.e., near the end of the month that VIVITROL was administered), or after a dose of VIVITROL is missed. It is important that patients inform family members and the people closest to the patient of this increased sensitivity to opioids and the risk of overdose [see Patient Counseling Information (17)].

There is also the possibility that a patient who is treated with VIVITROL could overcome the opioid blockade effect of VIVITROL. Although VIVITROL is a potent antagonist with a prolonged pharmacological effect, the blockade produced by VIVITROL is surmountable. The plasma concentration of exogenous opioids attained immediately following their acute administration may be sufficient to overcome the competitive receptor blockade. This poses a potential risk to individuals who attempt, on their own, to overcome the blockade by administering large amounts of exogenous opioids. Any attempt by a patient to overcome the antagonism by taking opioids is especially dangerous and may lead to life-threatening opioid intoxication or fatal overdose. Patients should be told of the serious consequences of trying to overcome the opioid blockade [see Patient Counseling Information (17)].

Patient Access to an Opioid Overdose Reversal Agent for the Emergency Treatment of Opioid Overdose

At the initial VIVITROL injection and with each subsequent injection, inform patients and caregivers about opioid overdose reversal agents (e.g., naloxone, nalmefene) and discuss the importance of having access to an opioid overdose reversal agent. Because of the risks for opioid overdose described above, both at the initial VIVITROL injection and with each subsequent injection, strongly consider recommending or prescribing an opioid overdose reversal agent for the emergency treatment of an opioid overdose.

Discuss the options for obtaining an opioid overdose reversal agent (e.g., prescription, over-the-counter, or as part of a community-based program).

There are important differences among the opioid overdose reversal agents, such as route of administration, product strength, approved patient age range, and pharmacokinetics. Be familiar with these differences, as outlined in the approved labeling for those products, prior to recommending or prescribing such an agent.

Educate patients and caregivers on how to recognize the signs and symptoms of an opioid overdose and how to use an opioid overdose reversal agent for the emergency treatment of opioid overdose. Emphasize the importance of calling 911 or getting emergency medical help in all cases of known or suspected opioid overdose, even if an opioid overdose reversal agent is administered.

5.2 Injection Site Reactions

VIVITROL must be prepared and administered by a healthcare provider.

VIVITROL must ONLY be administered as a deep intramuscular gluteal injection.

VIVITROL injections may be followed by pain, tenderness, induration, swelling, erythema, bruising, or pruritus; however, in some cases injection site reactions may be very severe. In the clinical trials, one patient developed an area of induration that continued to enlarge after 4 weeks, with subsequent development of necrotic tissue that required surgical excision. In the postmarketing period, additional cases of injection site reaction with features including induration, cellulitis, hematoma, abscess, sterile abscess, and necrosis, have been reported. Some cases required surgical intervention, including debridement of necrotic tissue. Some cases resulted in significant scarring. The reported cases occurred primarily in female patients.

VIVITROL is administered as a deep intramuscular gluteal injection, and inadvertent subcutaneous injection of VIVITROL may increase the likelihood of severe injection site reactions. The needles provided in the carton are customized needles. VIVITROL must not be injected using any other needle. The needle lengths (either 1 1/2 or 2 inches) may not be adequate in every patient because of body habitus. Body habitus should be assessed prior to each injection for each patient to assure that the proper needle is selected and that the needle length is adequate for intramuscular administration. For patients with a larger amount of subcutaneous tissue overlying the gluteal muscle, the administering healthcare provider may utilize the supplied 2-inch needle with needle protection device to help ensure that the injectate reaches the intramuscular mass. For very lean patients, the 1 1/2-inch needle may be appropriate to prevent the needle contacting the periosteum. Either needle may be used for patients with average body habitus. Healthcare providers should ensure that the VIVITROL injection is given correctly, and should consider alternate treatment for those patients whose body habitus precludes an intramuscular gluteal injection with one of the provided needles.

Patients should be informed that any concerning injection site reactions should be brought to the attention of the healthcare provider [see Patient Counseling Information (17)]. Patients exhibiting signs of abscess, cellulitis, necrosis, or extensive swelling should be evaluated by a physician to determine if referral to a surgeon is warranted.

5.3 Precipitation of Opioid Withdrawal

The symptoms of spontaneous opioid withdrawal (which are associated with the discontinuation of opioid in a dependent individual) are uncomfortable, but they are not generally believed to be severe or necessitate hospitalization. However, when withdrawal is precipitated abruptly by the administration of an opioid antagonist to an opioid-dependent patient, the resulting withdrawal syndrome can be severe enough to require hospitalization. Review of postmarketing cases of precipitated opioid withdrawal in association with naltrexone treatment has identified cases with symptoms of withdrawal severe enough to require hospital admission, and in some cases, management in the intensive care unit.

To prevent occurrence of precipitated withdrawal in patients dependent on opioids, or exacerbation of a pre-existing subclinical withdrawal syndrome, opioid-dependent patients, including those being treated for alcohol dependence, should be opioid-free (including tramadol) before starting VIVITROL treatment. An opioid-free interval of a minimum of 7–10 days is recommended for patients previously dependent on short-acting opioids. Patients transitioning from buprenorphine or methadone may be vulnerable to precipitation of withdrawal symptoms for as long as two weeks.

If a more rapid transition from agonist to antagonist therapy is deemed necessary and appropriate by the healthcare provider, monitor the patient closely in an appropriate medical setting where precipitated withdrawal can be managed.

In every case, healthcare providers should always be prepared to manage withdrawal symptomatically with non-opioid medications because there is no completely reliable method for determining whether a patient has had an adequate opioid-free period. A naloxone challenge test may be helpful; however, a few case reports have indicated that patients may experience precipitated withdrawal despite having a negative urine toxicology screen or tolerating a naloxone challenge test (usually in the setting of transitioning from buprenorphine treatment). Patients should be made aware of the risks associated with precipitated withdrawal and encouraged to give an accurate account of last opioid use. Patients treated for alcohol dependence with VIVITROL should also be assessed for underlying opioid dependence and for any recent use of opioids prior to initiation of treatment with VIVITROL. Precipitated opioid withdrawal has been observed in alcohol-dependent patients in circumstances where the prescriber had been unaware of the additional use of opioids or co-dependence on opioids.

5.4 Hepatotoxicity

Cases of hepatitis and clinically significant liver dysfunction were observed in association with VIVITROL exposure during the clinical development program and in the postmarketing period. Transient, asymptomatic hepatic transaminase elevations were also observed in the clinical trials and postmarketing period. Although patients with clinically significant liver disease were not systematically studied, clinical trials did include patients with asymptomatic viral hepatitis infections. When patients presented with elevated transaminases, there were often other potential causative or contributory etiologies identified, including pre-existing alcoholic liver disease, hepatitis B and/or C infection, and concomitant usage of other potentially hepatotoxic drugs. Although clinically significant liver dysfunction is not typically recognized as a manifestation of opioid withdrawal, opioid withdrawal that is precipitated abruptly may lead to systemic sequelae including acute liver injury.

Patients should be warned of the risk of hepatic injury and advised to seek medical attention if they experience symptoms of acute hepatitis. Use of VIVITROL should be discontinued in the event of symptoms and/or signs of acute hepatitis.

5.5 Depression and Suicidality

Alcohol- and opioid-dependent patients, including those taking VIVITROL, should be monitored for the development of depression or suicidal thinking. Families and caregivers of patients being treated with VIVITROL should be alerted to the need to monitor patients for the emergence of symptoms of depression or suicidality, and to report such symptoms to the patient's healthcare provider.

Alcohol Dependence

In controlled clinical trials of VIVITROL administered to adults with alcohol dependence, adverse events of a suicidal nature (suicidal ideation, suicide attempts, completed suicides) were infrequent overall, but were more common in patients treated with VIVITROL than in patients treated with placebo (1% vs 0%). In some cases, the suicidal thoughts or behavior occurred after study discontinuation, but were in the context of an episode of depression that began while the patient was on study drug. Two completed suicides occurred, both involving patients treated with VIVITROL.

Depression-related events associated with premature discontinuation of study drug were also more common in patients treated with VIVITROL (~1%) than in placebo-treated patients (0%).

In the 24-week, placebo-controlled pivotal trial in 624 alcohol-dependent patients, adverse events involving depressed mood were reported by 10% of patients treated with VIVITROL 380 mg, as compared to 5% of patients treated with placebo injections.

Opioid Dependence

In an open-label, long-term safety study conducted in the US, adverse events of a suicidal nature (depressed mood, suicidal ideation, suicide attempt) were reported by 5% of opioid-dependent patients treated with VIVITROL 380 mg (n=101) and 10% of opioid-dependent patients treated with oral naltrexone (n=20). In the 24-week, placebo-controlled pivotal trial that was conducted in Russia in 250 opioid-dependent patients, adverse events involving depressed mood or suicidal thinking were not reported by any patient in either treatment group (VIVITROL 380 mg or placebo).

5.6 When Reversal of VIVITROL Blockade Is Required for Pain Management

In an emergency situation in patients receiving VIVITROL, suggestions for pain management include regional analgesia or use of non-opioid analgesics. If opioid therapy is required as part of anesthesia or analgesia, patients should be continuously monitored in an anesthesia care setting by persons not involved in the conduct of the surgical or diagnostic procedure. The opioid therapy must be provided by individuals specifically trained in the use of anesthetic drugs and the management of the respiratory effects of potent opioids, specifically the establishment and maintenance of a patent airway and assisted ventilation.

Irrespective of the drug chosen to reverse VIVITROL blockade, the patient should be monitored closely by appropriately trained personnel in a setting equipped and staffed for cardiopulmonary resuscitation.

5.7 Eosinophilic Pneumonia

In clinical trials with VIVITROL, there was one diagnosed case and one suspected case of eosinophilic pneumonia. Both cases required hospitalization, and resolved after treatment with antibiotics and corticosteroids. Similar cases have been reported in postmarketing use. Should a person receiving VIVITROL develop progressive dyspnea and hypoxemia, the diagnosis of eosinophilic pneumonia should be considered [see Adverse Reactions (6)]. Patients should be warned of the risk of eosinophilic pneumonia, and advised to seek medical attention should they develop symptoms of pneumonia. Clinicians should consider the possibility of eosinophilic pneumonia in patients who do not respond to antibiotics.

5.8 Hypersensitivity Reactions Including Anaphylaxis

Cases of urticaria, angioedema, and anaphylaxis have been observed with use of VIVITROL in the clinical trial setting and in postmarketing use. Patients should be warned of the risk of hypersensitivity reactions, including anaphylaxis. In the event of a hypersensitivity reaction, patients should be advised to seek immediate medical attention in a healthcare setting prepared to treat anaphylaxis. The patient should not receive any further treatment with VIVITROL.

5.9 Intramuscular Injections

As with any intramuscular injection, VIVITROL should be administered with caution to patients with thrombocytopenia or any coagulation disorder (e.g., hemophilia and severe hepatic failure).

5.10 Alcohol Withdrawal

Use of VIVITROL does not eliminate nor diminish alcohol withdrawal symptoms.

5.11 Interference with Laboratory Tests

VIVITROL may be cross-reactive with certain immunoassay methods for the detection of drugs of abuse (specifically opioids) in urine. For further information, reference to the specific immunoassay instructions is recommended.

6 ADVERSE REACTIONS

The following clinically significant adverse reactions are described elsewhere in the labeling:

- Accidental Opioid Overdose [see Warnings and Precautions (5.1)]
- Injection Site Reactions [see Warnings and Precautions (5.2)]
- Precipitated Opioid Withdrawal [see Warnings and Precautions (5.3)]
- Hepatotoxicity [see Warnings and Precautions (5.4)]
- Depression and Suicidality [see Warnings and Precautions (5.5)]
- Eosinophilic Pneumonia [see Warnings and Precautions (5.7)]
- Hypersensitivity Reactions [see Warnings and Precautions (5.8)]

6.1 Clinical Trials Experience

Because clinical trials are conducted under widely varying conditions, adverse reaction rates observed in the clinical trials of a drug cannot be directly compared to rates in the clinical trials of another drug and may not reflect the rates observed in practice.

In all controlled and uncontrolled trials during the premarketing development of VIVITROL, more than 1100 patients with alcohol and/or opioid dependence have been treated with VIVITROL. Approximately 700 patients have been treated for 6 months or more, and more than 400 for 1 year or longer.

Adverse Events Leading to Discontinuation of Treatment

Alcohol Dependence

In controlled trials of 6 months or less in alcohol-dependent patients, 9% of alcohol-dependent patients treated with VIVITROL discontinued treatment due to an adverse event, as compared to 7% of the alcohol-dependent patients treated with placebo. Adverse events in the VIVITROL 380 mg group that led to more dropouts than in the placebo-treated group were injection site reactions (3%), nausea (2%), pregnancy (1%), headache (1%), and suicide-related events (0.3%). In the placebo group, 1% of patients withdrew due to injection site reactions, and 0% of patients withdrew due to the other adverse events.

Opioid Dependence

In a controlled trial of 6 months, 2% of opioid-dependent patients treated with VIVITROL discontinued treatment due to an adverse event, as compared to 2% of the opioid-dependent patients treated with placebo.

Common Adverse Reactions

Alcohol Dependence

Table 1 lists all treatment-emergent clinical adverse reactions, regardless of causality, occurring in ≥5% of patients with alcohol dependence, for which the incidence was greater in the combined VIVITROL group than in the placebo group. A majority of patients treated with VIVITROL in clinical studies had adverse reactions with a maximum intensity of “mild” or “moderate”.

Table 1: Treatment-emergent Adverse Reactions (Reactions in ≥5% of patients with alcohol dependence treated with VIVITROL and occurring more frequently in the combined VIVITROL group than in the placebo group)
Body System | Adverse Reaction / Preferred Term | Placebo |  | Naltrexone for extended-release injectable suspension
Body System | Adverse Reaction / Preferred Term | N=214 |  | 400 mg N=25 |  | 380 mg N=205 |  | 190 mg N=210 |  | All N=440
Body System | Adverse Reaction / Preferred Term | N | % | N | % | N | % | N | % | N | %
Gastrointestinal Disorders | Nausea | 24 | 11 | 8 | 32 | 68 | 33 | 53 | 25 | 129 | 29
Gastrointestinal Disorders | Vomiting NOS | 12 | 6 | 3 | 12 | 28 | 14 | 22 | 10 | 53 | 12
Gastrointestinal Disorders | Diarrheaa) | 21 | 10 | 3 | 12 | 27 | 13 | 27 | 13 | 57 | 13
Gastrointestinal Disorders | Abdominal painb) | 17 | 8 | 4 | 16 | 23 | 11 | 23 | 11 | 50 | 11
 | Dry Mouth | 9 | 4 | 6 | 24 | 10 | 5 | 8 | 4 | 24 | 5
Infections & Infestations | Pharyngitisc) | 23 | 11 | 0 | 0 | 22 | 11 | 35 | 17 | 57 | 13
Psychiatric Disorders | Insomnia, sleep disorder | 25 | 12 | 2 | 8 | 29 | 14 | 27 | 13 | 58 | 13
Psychiatric Disorders | Anxietyd) | 17 | 8 | 2 | 8 | 24 | 12 | 16 | 8 | 42 | 10
Psychiatric Disorders | Depression | 9 | 4 | 0 | 0 | 17 | 8 | 7 | 3 | 24 | 5
General Disorders & Administration Site Conditions | Any ISR | 106 | 50 | 22 | 88 | 142 | 69 | 121 | 58 | 285 | 65
General Disorders & Administration Site Conditions | Injection site tenderness | 83 | 39 | 18 | 72 | 92 | 45 | 89 | 42 | 199 | 45
General Disorders & Administration Site Conditions | Injection site induration | 18 | 8 | 7 | 28 | 71 | 35 | 52 | 25 | 130 | 30
General Disorders & Administration Site Conditions | Injection site pain | 16 | 7 | 0 | 0 | 34 | 17 | 22 | 10 | 56 | 13
General Disorders & Administration Site Conditions | Other ISR (primarily nodules, swelling) | 8 | 4 | 8 | 32 | 30 | 15 | 16 | 8 | 54 | 12
General Disorders & Administration Site Conditions | Injection site pruritus | 0 | 0 | 0 | 0 | 21 | 10 | 13 | 6 | 34 | 8
General Disorders & Administration Site Conditions | Injection site ecchymosis | 11 | 5 | 0 | 0 | 14 | 7 | 9 | 4 | 23 | 5
General Disorders & Administration Site Conditions | Asthenic conditionse) | 26 | 12 | 3 | 12 | 47 | 23 | 40 | 19 | 90 | 20
Musculoskeletal & Connective Tissue Disorders | Arthralgia, arthritis, joint stiffness | 11 | 5 | 1 | 4 | 24 | 12 | 12 | 6 | 37 | 9
Musculoskeletal & Connective Tissue Disorders | Back pain, back stiffness | 10 | 5 | 1 | 4 | 12 | 6 | 14 | 7 | 27 | 6
Musculoskeletal & Connective Tissue Disorders | Muscle crampsf) | 3 | 1 | 0 | 0 | 16 | 8 | 5 | 2 | 21 | 5
Skin & Subcutaneous Tissue Disorders | Rashg) | 8 | 4 | 3 | 12 | 12 | 6 | 10 | 5 | 25 | 6
Nervous System Disorders | Headacheh) | 39 | 18 | 9 | 36 | 51 | 25 | 34 | 16 | 94 | 21
Nervous System Disorders | Dizziness, syncope | 9 | 4 | 4 | 16 | 27 | 13 | 27 | 13 | 58 | 13
Nervous System Disorders | Somnolence, sedation | 2 | 1 | 3 | 12 | 8 | 4 | 9 | 4 | 20 | 5
Metabolism & Nutrition Disorders | Anorexia, appetite decreased NOS, appetite disorder NOS | 6 | 3 | 5 | 20 | 30 | 14 | 13 | 6 | 48 | 11
a) Includes the preferred terms: diarrhea NOS; frequent bowel movements; gastrointestinal upset; loose stools
b) Includes the preferred terms: abdominal pain NOS; abdominal pain upper; stomach discomfort; abdominal pain lower
c) Includes the preferred terms: nasopharyngitis; pharyngitis streptococcal; pharyngitis NOS
d) Includes the preferred terms: anxiety NEC; anxiety aggravated; agitation; obsessive compulsive disorder; panic attack; nervousness; posttraumatic stress
e) Includes the preferred terms: malaise; fatigue (these two comprise the majority of cases); lethargy; sluggishness
f) Includes the preferred terms: muscle cramps; spasms; tightness; twitching; stiffness; rigidity
g) Includes the preferred terms: rash NOS; rash papular; heat rash
h) Includes the preferred terms: headache NOS; sinus headache; migraine; frequent headaches

Opioid Dependence

In the open-label, long-term safety study conducted in the US, the commonly reported adverse reactions among the opioid-dependent patients in the study were similar to those commonly observed events in the alcohol-dependent populations in VIVITROL clinical trials as displayed in Table 1, above. For example, injection site reactions of all types, nausea and diarrhea occurred in more than 5% of patients on VIVITROL in the open-label study. In contrast, 48% percent, of the opioid-dependent patients had at least one adverse event in the “Infections and Infestations” Body System. Adverse Reactions/Preferred Terms of nasopharyngitis, upper respiratory tract infection, urinary tract infection, and sinusitis were most commonly reported.

In the placebo-controlled study in opioid-dependent patients conducted in Russia, the overall frequency of adverse events was lower than in the U.S. population described above. Table 2 lists treatment-emergent clinical adverse events, regardless of causality, occurring in ≥2% of patients with opioid dependence, for which the incidence was greater in the VIVITROL group than in the placebo group. All adverse events were assessed as having a maximum intensity of “mild” or “moderate.”

Table 2: Treatment-emergent Clinical Adverse Events (Events in ≥2% of patients with opioid dependence treated with VIVITROL and occurring more frequently in the VIVITROL group than in the placebo group)
Body System | Adverse Event / Preferred Term | Placebo N=124 |  | VIVITROL 380 mg N=126
Body System | Adverse Event / Preferred Term | n | % | n | %
Investigations | Alanine aminotransferase increased | 7 | 6 | 16 | 13
Investigations | Aspartate aminotransferase increased | 3 | 2 | 13 | 10
Investigations | Gamma-glutamyltransferase increased | 4 | 3 | 9 | 7
Infections and Infestations | Nasopharyngitis | 3 | 2 | 9 | 7
Infections and Infestations | Influenza | 5 | 4 | 6 | 5
Psychiatric Disorders | Insomnia | 1 | 1 | 8 | 6
Vascular Disorders | Hypertension | 4 | 3 | 6 | 5
General Disorders and Administration Site Conditions | Injection site pain | 1 | 1 | 6 | 5
Gastrointestinal Disorders | Toothache | 2 | 2 | 5 | 4
Nervous System Disorders | Headache | 3 | 2 | 4 | 3

Laboratory Tests

Eosinophil Count

In clinical trials, subjects on VIVITROL had increases in eosinophil counts relative to subjects on placebo. With continued use of VIVITROL, eosinophil counts returned to normal over a period of several months.

Platelet Count

VIVITROL 380 mg was associated with a decrease in platelet count. In clinical trials, alcohol-dependent patients treated with VIVITROL experienced a mean maximal decrease in platelet count of 17.8 × 10^3/μL, compared to 2.6 × 10^3/μL in placebo patients.

After 24 weeks of treatment, opioid-dependent patients treated with VIVITROL experienced a mean maximal decrease in platelet count of 62.8 × 10^3/μL, compared to 39.9 × 10^3/μL in placebo patients. In randomized controlled trials, VIVITROL was not associated with an increase in bleeding-related adverse events.

Hepatic Enzyme Elevations

In short-term, controlled trials, in alcohol-dependent patients, the incidence of AST elevations associated with VIVITROL treatment was similar to that observed with oral naltrexone treatment (1.5% each) and slightly higher than observed with placebo treatment (0.9%).

In the 6-month controlled trial conducted in opioid-dependent subjects, 89% had a baseline diagnosis of hepatitis C infection, and 41% had a baseline diagnosis of HIV infection. There were frequently observed elevated liver enzyme levels (ALT, AST, and GGT); these were more commonly reported as adverse events in the VIVITROL 380 mg group than in the placebo group. Patients could not enroll in this trial if they had a baseline ALT or AST value that was more than three times the upper limit of normal. More patients treated with VIVITROL in this study experienced treatment-emergent elevations in transaminases to more than three times the upper limit of normal than patients treated with placebo. Shifts to more than three times the upper limit of normal occurred in 20% of patients treated with VIVITROL as compared with 13% of placebo patients. Shifts in values of AST to more than three times the upper limit were also more common in the VIVITROL (14%) arm compared with the placebo (11%) arm. Opioid-dependent patients treated with VIVITROL experienced a mean maximal increase from baseline ALT levels of 61 IU/L compared with 48 IU/L in placebo patients. Similarly for AST, opioid-dependent patients treated with VIVITROL experienced a mean maximal increase from baseline AST levels of 40 IU/L compared with 31 IU/L in placebo patients.

Creatinine Phosphokinase

In short-term controlled trials in alcohol-dependent patients, more patients treated with VIVITROL 380 mg (11%) and oral naltrexone (17%) shifted from normal creatinine phosphokinase (CPK) levels before treatment to abnormal CPK levels at the end of the trials, compared to placebo patients (8%). In open-label trials, 16% of patients dosed for more than 6 months had increases in CPK. For both the oral naltrexone and VIVITROL 380 mg groups, CPK abnormalities were most frequently in the range of 1–2 × ULN. However, there were reports of CPK abnormalities as high as 4x ULN for the oral naltrexone group, and 35 × ULN for the VIVITROL 380 mg group. Overall, there were no differences between the placebo and naltrexone (oral or injectable) groups with respect to the proportions of patients with a CPK value at least three times the upper limit of normal. No factors other than naltrexone exposure were associated with the CPK elevations.

More opioid-dependent patients treated with VIVITROL 380 mg (39%) shifted from normal creatinine phosphokinase (CPK) levels before treatment to abnormal CPK levels during the study as compared to patients treated with placebo (32%). There were reports of CPK abnormalities as high as 41.8 × ULN for the placebo group, and 22.1 × ULN for the VIVITROL 380 mg group.

Other Events Observed During the VIVITROL Clinical Studies

The following is a list of treatment-emergent adverse reactions reported by alcohol- and/or opioid-dependent subjects treated with VIVITROL in all clinical trials. The listing does not include those events already listed in the previous tables or elsewhere in labeling, those events for which a drug cause was remote, those events that were so general as to be uninformative, and those events reported only once that did not have a substantial probability of being acutely life-threatening.

Blood and Lymphatic System Disorders – lymphadenopathy (including cervical adenitis), white blood cell count increased

Cardiac Disorders – angina pectoris, angina unstable, atrial fibrillation, cardiac failure congestive, coronary artery atherosclerosis, myocardial infarction, palpitations

Eye Disorders – conjunctivitis, vision blurred

Gastrointestinal Disorders – abdominal discomfort, colitis, constipation, flatulence, gastroesophageal reflux disease, gastrointestinal hemorrhage, hemorrhoids, pancreatitis acute, paralytic ileus, perirectal abscess

General Disorders and Administration Site Conditions – chest pain, chest tightness, chills, face edema, irritability, lethargy, pyrexia, rigors

Hepatobiliary Disorders – cholecystitis acute, cholelithiasis

Immune System Disorders – seasonal allergy, hypersensitivity reaction (including angioneurotic edema and urticaria)

Infections and Infestations – bronchitis, gastroenteritis, laryngitis, pneumonia, sinusitis, tooth abscess, upper respiratory tract infection, urinary tract infection, advanced HIV disease in HIV-infected patients

Investigations – weight decreased, weight increased

Metabolism and Nutrition Disorders – appetite increased, dehydration, heat exhaustion, hypercholesterolemia

Musculoskeletal and Connective Tissue Disorders – joint stiffness, muscle spasms, myalgia, pain in limb

Nervous System Disorders – cerebral arterial aneurysm, convulsions, disturbance in attention, dysgeusia, mental impairment, migraine, ischemic stroke, paresthesia

Pregnancy, Puerperium, and Perinatal Conditions – abortion missed

Psychiatric Disorders – abnormal dreams, agitation, alcohol withdrawal syndrome, euphoric mood, delirium, libido decreased

Respiratory, Thoracic, and Mediastinal Disorders – chronic obstructive pulmonary disease, dyspnea, pharyngolaryngeal pain, sinus congestion

Skin and Subcutaneous Tissue Disorders – night sweats, pruritus, sweating increased

Vascular Disorders – deep venous thrombosis, hot flushes, pulmonary embolism

6.2 Postmarketing Experience

Adverse Events Following Patient Self-Administration

Adverse events including injection site reactions and precipitated opioid withdrawal resulting in serious outcomes, including hospitalization, have been reported following patient self-administration of VIVITROL. VIVITROL must be prepared and administered by a healthcare provider.

Hypersensitivity Reactions Including Anaphylaxis

Hypersensitivity reactions including anaphylaxis have been reported during postmarketing surveillance.

Reports From Other Intramuscular Drug Products Containing Polylactide-co-glycolide (PLG) Microspheres

Retinal Artery Occlusion

Retinal artery occlusion after injection with another drug product containing polylactide-co-glycolide (PLG) microspheres has been reported very rarely during postmarketing surveillance. This event has been reported in the presence of abnormal arteriovenous anastomosis. No cases of retinal artery occlusion have been reported during VIVITROL clinical trials or postmarketing surveillance. VIVITROL should be administered by intramuscular (IM) injection into the gluteal muscle, and care must be taken to avoid inadvertent injection into a blood vessel [see Dosage and Administration (2)].

7 DRUG INTERACTIONS

Patients taking VIVITROL may not benefit from opioid-containing medicines. Naltrexone antagonizes the effects of opioid-containing medicines, such as cough and cold remedies, antidiarrheal preparations and opioid analgesics.

8 USE IN SPECIFIC POPULATIONS

8.1 Pregnancy

Risk Summary

The available data from published case series with VIVITROL use in pregnant women are insufficient to identify a drug-associated risk of major birth defects, miscarriage or adverse maternal or fetal outcomes. There are clinical considerations (see Clinical Considerations). Reproduction and developmental animal studies have not been conducted for VIVITROL. Daily oral administration of naltrexone to female rats and rabbits increased the incidence of early fetal loss at exposures ≥ 11 times and ≥ 2 times the human exposure, respectively. Daily oral administration of naltrexone to pregnant rats and rabbits during the period of organogenesis did not induce malformation at exposures up to 175 times and 14 times the human exposure, respectively (see Data).

The estimated background risk of major birth defects and miscarriage for the indicated population is unknown. All pregnancies have a background risk of birth defect, loss, or other adverse outcomes. In the U.S. general population, the estimated background risk of major birth defects and miscarriage in clinically recognized pregnancies is 2% to 4% and 15% to 20%, respectively.

Clinical Considerations

Disease-associated maternal and embryo-fetal risk

Untreated opioid addiction in pregnancy is associated with adverse obstetrical outcomes such as low birth weight, preterm birth, and fetal death. In addition, untreated opioid addiction often results in continued or relapsing illicit opioid use.

Published studies have demonstrated that alcohol is associated with fetal harm including growth restriction, facial abnormalities, central nervous system abnormalities, behavioral disorders, and impaired intellectual development.

Data

Animal Data

Reproduction and developmental studies have not been conducted for VIVITROL. Studies with naltrexone administered via the oral route have been conducted in pregnant rats and rabbits.

Daily oral administration of naltrexone has been shown to increase the incidence of early fetal loss when given to rats at doses ≥30 mg/kg/day (11 times the human exposure based on an AUC(0-28d) comparison) and to rabbits at oral doses ≥60 mg/kg/day (2 times the human exposure based on an AUC(0-28d) comparison).

Daily oral administration of naltrexone to rats and rabbits during the period of organogenesis did not induce malformations at doses up to 200 mg/kg/day (175- and 14-times the human exposure based on an AUC(0-28d) comparison, respectively).

8.2 Lactation

Risk Summary

Naltrexone and its major metabolite, 6β-naltrexol, are present in human milk. There are no data on the effects on the breastfed infant or the effects on milk production. The developmental health benefits of breastfeeding should be considered along with the mother's clinical need for naltrexone and any potential adverse effects on the breastfed infant from naltrexone or the mother's underlying maternal condition.

8.4 Pediatric Use

The safety and efficacy of VIVITROL have not been established in the pediatric population. The pharmacokinetics of VIVITROL have not been evaluated in a pediatric population.

8.5 Geriatric Use

In trials of alcohol-dependent subjects, 2.6% (n=26) of subjects were >65 years of age, and one patient was >75 years of age. Clinical studies of VIVITROL did not include sufficient numbers of subjects age 65 and over to determine whether they respond differently from younger subjects. No subjects over age 65 were included in studies of opioid-dependent subjects. The pharmacokinetics of VIVITROL have not been evaluated in the geriatric population.

This drug is known to be substantially excreted by the kidney, and the risk of adverse reactions to this drug may be greater in patients with impaired renal function. Because elderly patients are more likely to have decreased renal function, it may be useful to monitor renal function.

8.6 Renal Impairment

Pharmacokinetics of VIVITROL are not altered in subjects with mild renal insufficiency (creatinine clearance of 50-80 mL/min). Dose adjustment is not required in patients with mild renal impairment. VIVITROL pharmacokinetics have not been evaluated in subjects with moderate and severe renal insufficiency. Because naltrexone and its primary metabolite are excreted primarily in the urine, caution is recommended in administering VIVITROL to patients with moderate to severe renal impairment [see Clinical Pharmacology (12.3)].

8.7 Hepatic Impairment

The pharmacokinetics of VIVITROL are not altered in subjects with mild to moderate hepatic impairment (Groups A and B of the Child-Pugh classification). Dose adjustment is not required in subjects with mild or moderate hepatic impairment. VIVITROL pharmacokinetics were not evaluated in subjects with severe hepatic impairment [see Clinical Pharmacology (12.3)].

10 OVERDOSAGE

There is limited experience with overdose of VIVITROL. Single doses up to 784 mg were administered to 5 healthy subjects. There were no serious or severe adverse events. The most common effects were injection site reactions, nausea, abdominal pain, somnolence, and dizziness. There were no significant increases in hepatic enzymes.

In the event of an overdose, appropriate supportive treatment should be initiated.

11 DESCRIPTION

VIVITROL® (naltrexone for extended-release injectable suspension) is supplied as a microsphere formulation of naltrexone for suspension, to be administered by deep intramuscular injection by a healthcare practitioner. VIVITROL contains naltrexone base anhydrous as the active pharmaceutical ingredient. Naltrexone is an opioid antagonist with little, if any, opioid agonist activity.

Naltrexone is morphinan-6-one, 17-(cyclopropylmethyl)-4,5-epoxy-3,14-dihydroxy-(5α) (CAS Registry # 16590-41-3). The molecular formula is C20H23NO4 and its molecular weight is 341.41 in the anhydrous form (ie, < 1% maximum water content). The structural formula is:

Naltrexone base anhydrous is an off-white to a light tan powder with a melting point of 168 °C to 170 °C (334 °F to 338 °F). It is insoluble in water and is soluble in ethanol.

VIVITROL is provided in a carton containing one vial of VIVITROL microspheres, one vial of diluent, one 5-mL syringe, one 1-inch 20-gauge preparation needle, two 1 1/2-inch 20-gauge, and two 2-inch 20-gauge administration needles with needle protection device.

VIVITROL microspheres consist of a sterile, off-white to light tan powder that is available in a dosage strength of 380 mg of naltrexone per vial. Naltrexone base anhydrous is incorporated in a biodegradable matrix of 75:25 polylactide-co-glycolide (PLG) at a concentration of 337 mg of naltrexone per gram of microspheres.

The diluent is a clear, colorless solution. Each mL of diluent contains 30.0 mg of carboxymethylcellulose sodium, 1.0 mg of polysorbate 20, 9.0 mg of sodium chloride, and sodium hydroxide and hydrochloric acid as pH adjusters, in water for injection. The pH of the diluent is in the range of 5.8 to 7.2.

12 CLINICAL PHARMACOLOGY

12.1 Mechanism of Action

Naltrexone is an opioid antagonist with highest affinity for the mu opioid receptor. Naltrexone has little or no opioid agonist activity.

12.2 Pharmacodynamics

Naltrexone has few, if any, intrinsic actions besides its opioid blocking properties. However, it does produce some pupillary constriction, by an unknown mechanism.

The administration of VIVITROL is not associated with the development of tolerance or dependence. In subjects physically dependent on opioids, VIVITROL will precipitate withdrawal symptomatology.

Occupation of opioid receptors by naltrexone may block the effects of endogenous opioid peptides. It markedly attenuates or completely blocks, reversibly, the subjective effects of exogenous opioids. The neurobiological mechanisms responsible for the reduction in alcohol consumption observed in alcohol-dependent patients treated with naltrexone are not entirely understood. However, involvement of the endogenous opioid system is suggested by preclinical data.

Naltrexone blocks the effects of opioids by competitive binding at opioid receptors. This makes the blockade produced potentially surmountable, but overcoming full naltrexone blockade by administration of opioids may result in non-opioid receptor-mediated symptoms such as histamine release.

VIVITROL is not aversive therapy and does not cause a disulfiram-like reaction either as a result of opioid use or ethanol ingestion.

12.3 Pharmacokinetics

Absorption

VIVITROL is an extended-release, microsphere formulation of naltrexone designed to be administered by intramuscular (IM) gluteal injection every 4 weeks or once a month. After IM injection, the naltrexone plasma concentration time profile is characterized by a transient initial peak, which occurs approximately 2 hours after injection, followed by a second peak observed approximately 2-3 days later. Beginning approximately 14 days after dosing, concentrations slowly decline, with measurable levels for greater than 1 month.

Maximum plasma concentration (Cmax) and area under the curve (AUC) for naltrexone and 6β-naltrexol (the major metabolite) following VIVITROL administration are dose proportional. Compared to daily oral dosing with naltrexone 50 mg over 28 days, total naltrexone exposure is 3 to 4-fold higher following administration of a single dose of VIVITROL 380 mg. Steady state is reached at the end of the dosing interval following the first injection. There is minimal accumulation (<15%) of naltrexone or 6β-naltrexol upon repeat administration of VIVITROL.

Distribution

In vitro data demonstrate that naltrexone plasma protein binding is low (21%).

Elimination

The elimination half life of naltrexone following VIVITROL administration is 5-10 days and is dependent on the erosion of the polymer. The elimination half life of 6β-naltrexol following VIVITROL administration is 5-10 days.

Metabolism

Naltrexone is extensively metabolized in humans. Production of the primary metabolite, 6β-naltrexol, is mediated by dihydrodiol dehydrogenase, a cytosolic family of enzymes. The cytochrome P450 system is not involved in naltrexone metabolism. Two other minor metabolites are 2-hydroxy-3-methoxy-6β-naltrexol and 2-hydroxy-3-methoxy-naltrexone. Naltrexone and its metabolites are also conjugated to form glucuronide products.

Significantly less 6β-naltrexol is generated following IM administration of VIVITROL compared to administration of oral naltrexone due to a reduction in first-pass hepatic metabolism.

Excretion

Elimination of naltrexone and its metabolites occurs primarily via urine, with minimal excretion of unchanged naltrexone.

Specific Populations

Pediatric: Pharmacokinetics of VIVITROL have not been evaluated in a pediatric population.

Geriatric: Pharmacokinetics of VIVITROL have not been evaluated in the geriatric population [see Use in Specific Populations (8.5)].

Race: Effect of race on the pharmacokinetics of VIVITROL has not been studied.

Sex: In a study in healthy subjects (n=18 females and 18 males), sex did not influence the pharmacokinetics of VIVITROL.

Renal Insufficiency: A population pharmacokinetic analysis indicated mild renal insufficiency (creatinine clearance of 50-80 mL/min) had little or no influence on VIVITROL pharmacokinetics and that no dosage adjustment is necessary. VIVITROL pharmacokinetics have not been evaluated in subjects with moderate and severe renal insufficiency [see Use in Specific Populations (8.6)].

Hepatic Insufficiency: The pharmacokinetics of VIVITROL are not altered in subjects with mild to moderate hepatic impairment (Groups A and B of the Child-Pugh classification). VIVITROL pharmacokinetics were not evaluated in subjects with severe hepatic impairment [see Use in Specific Populations (8.7)].

Drug Interactions

In Vitro Studies: Because naltrexone is not a substrate for CYP drug metabolizing enzymes, inducers or inhibitors of these enzymes are unlikely to change the clearance of VIVITROL. An in vitro CYP inhibition study demonstrated that naltrexone is not an inhibitor of major CYP enzymes (CYP 1A2, 2A6, 2B6, 2C8, 2C9, 2C19, 2D6, 2E1, 3A4). An in vitro CYP induction study demonstrated that naltrexone is not an inducer of CYP3A4 and CYP1A2.

13 NONCLINICAL TOXICOLOGY

13.1 Carcinogenesis, Mutagenesis, Impairment of Fertility

Carcinogenesis: Carcinogenicity studies have not been conducted with VIVITROL.

Carcinogenicity studies of oral naltrexone hydrochloride (administered via the diet) have been conducted in rats and mice.

In a two-year carcinogenicity study in rats, there were small increases in the numbers of testicular mesotheliomas in males and tumors of vascular origin in males and females. The incidence of testicular mesothelioma in males given naltrexone at a dietary dose of 100 mg/kg/day (3-times the human exposure based on an AUC(0-28d) comparison) was 6%, compared with a maximum historical incidence of 4%. The incidence of vascular tumors in males and females given dietary doses of 100 mg/kg/day was 4% but only the incidence in females was increased compared with a maximum historical control incidence of 2% (3 and 32 times the human exposure based on an AUC(0-28d) comparison in males and females, respectively). There was no evidence of carcinogenicity in a 2-year dietary study with naltrexone in male and female mice (12 and 3 times the human exposure based on an AUC(0-28d) comparison, respectively). The clinical significance of these findings is not known.

Mutagenesis: Naltrexone was negative in the following in vitro genotoxicity studies: bacterial reverse mutation assay (Ames test), the heritable translocation assay, CHO cell sister chromatid exchange assay, and the mouse lymphoma gene mutation assay. Naltrexone was also negative in an in vivo mouse micronucleus assay. In contrast, naltrexone tested positive in the following assays: Drosophila recessive lethal frequency assay, non-specific DNA damage in repair tests with E. coli and WI-38 cells, and urinalysis for methylated histidine residues.

Impairment of Fertility: Daily oral administration of naltrexone caused a significant increase in pseudopregnancy and a decrease in pregnancy rates in rats at 100 mg/kg/day (75 times the human exposure based on an AUC(0-28d) comparison). There was no effect on male fertility at this dose level (6 times the human exposure based on an AUC(0-28d) comparison). The relevance of these observations to human fertility is not known.

14 CLINICAL STUDIES

Alcohol Dependence

The efficacy of VIVITROL in the treatment of alcohol dependence was evaluated in a 24-week, placebo-controlled, multi-center, double-blind, randomized trial of alcohol-dependent (DSM-IV criteria) outpatients. Subjects were treated with an injection every 4 weeks of VIVITROL 190 mg, VIVITROL 380 mg or placebo. Oral naltrexone was not administered prior to the initial or subsequent injections of study medication. Psychosocial support was provided to all subjects in addition to medication.

Subjects treated with VIVITROL 380 mg demonstrated a greater reduction in days of heavy drinking than those treated with placebo. Heavy drinking was defined as self-report of 5 or more standard drinks consumed on a given day for male patients and 4 or more drinks for female patients. Among the subset of patients (n=53, 8% of the total study population) who abstained completely from drinking during the week prior to the first dose of medication, compared with placebo-treated patients, those treated with VIVITROL 380 mg had greater reductions in the number of drinking days and the number of heavy drinking days. In this subset, patients treated with VIVITROL were also more likely than placebo-treated patients to maintain complete abstinence throughout treatment. The same treatment effects were not evident among the subset of patients (n=571, 92% of the total study population) who were actively drinking at the time of treatment initiation.

Opioid Dependence

The efficacy of VIVITROL in the treatment of opioid dependence was evaluated in a 24-week, placebo-controlled, multi-center, double-blind, randomized trial of opioid-dependent (DSM-IV) outpatients, who were completing or had recently completed detoxification. Subjects were treated with an injection every 4 weeks of VIVITROL 380 mg or placebo. Oral naltrexone was not administered prior to the initial or subsequent injections of study medication. Standardized, manual-based psychosocial support was provided on a biweekly basis to all subjects in addition to medication.

Figure 1, below, displays the cumulative percentage of subjects with opioid-free weeks ranging from no visits (0%) to all visits (100%). An opioid-free week was one in which urine drug test results were negative for opioids and self-reported opioid use was also zero. An initial period of engagement in treatment was permitted during which opiate use, if it occurred, was not considered in the analysis. Subjects discontinuing from the trial were assumed to have had opioid-use weeks for the weeks after dropout.

The cumulative percentage of subjects achieving each observed percentage of opioid-free weeks was greater in the VIVITROL group compared to the placebo group. Complete abstinence (opioid-free at all weekly visits) was sustained by 23% of subjects in the placebo group compared with 36% of subjects in the VIVITROL group from Week 5 to Week 24.

Figure 1: Subjects Sustaining Varying Percentages of Opioid-Free Weeks

A greater percentage of subjects in the VIVITROL group remained in the study compared to the placebo group.

16 HOW SUPPLIED/STORAGE AND HANDLING

VIVITROL (naltrexone for extended-release injectable suspension) is supplied in cartons (NDC 65757-300-01). Each carton contains:

- one 380 mg vial of VIVITROL microspheres in a 5 mL single-dose vial,
- one vial containing 4 mL of diluent (to deliver 3.4 mL) for the suspension of VIVITROL,
- one 5-mL prepackaged syringe,
- one 20-gauge 1-inch needle,
- two 20-gauge 1 1/2-inch needles with needle protection devices, and;
- two 20-gauge 2-inch needles with needle protection devices

VIVITROL must be prepared and administered by a healthcare provider.

16.1 Storage and Handling

The entire dose pack should be stored in the refrigerator (2 °C to 8 °C, 36 °F to 46 °F). Unrefrigerated, VIVITROL can be stored at temperatures not exceeding 25 °C (77 °F) for no more than 7 days prior to administration. Do not expose the product to temperatures above 25 °C (77 °F). VIVITROL should not be frozen.

Keep out of Reach of Children.

17 PATIENT COUNSELING INFORMATION

Advise the patient to read the FDA-Approved patient labeling (Medication Guide).

Physicians should include the following issues in discussions with patients for whom they prescribe VIVITROL.

VIVITROL for Opioid Use Disorder:

- Advise patients that if they previously used opioids, they may be more sensitive to lower doses of opioids and at risk of accidental overdose should they use opioids when their next dose is due, if they miss a dose, or after VIVITROL treatment is discontinued. It is important that patients inform family members and the people closest to the patient of this increased sensitivity to opioids and the risk of overdose. Educate patients and caregivers on how to recognize the signs and symptoms of an opioid overdose.
- Advise patients that because VIVITROL can block the effects of opioids, patients will not perceive any effect if they attempt to self-administer heroin or any other opioid drug in small doses while on VIVITROL. Further, emphasize that administration of large doses of heroin or any other opioid to try to bypass the blockade and get high while on VIVITROL may lead to serious injury, coma, or death.
- Patient Access to an Opioid Overdose Reversal Agent for the Emergency Treatment of Opioid Overdose
  Inform patients and caregivers about opioid overdose reversal agents (e.g., naloxone, nalmefene) and discuss the importance of having access to an opioid overdose reversal agent. Because of the vulnerability to opioid overdose described above, discuss with the patient and caregiver the importance of having access to an opioid overdose reversal agent [see Warnings and Precautions (5.1)].
  Discuss with the patient options for obtaining an opioid overdose reversal agent (e.g., prescription, over-the-counter (some products), or as part of a community-based program) [see Dosage and Administration (2.2), Warnings and Precautions (5.1)].
  There are important differences among the opioid overdose reversal agents. Be familiar with these differences, as outlined in the approved labeling for such products, prior to recommending or prescribing such an agent.
  Educate patients and caregivers on how to recognize the signs and symptoms of an opioid overdose.
  Explain to patients and caregivers that effects of opioid overdose reversal agents like naloxone and nalmefene are temporary, and that they must call 911 or get emergency medical help right away in all cases of known or suspected opioid overdose, even if an opioid overdose reversal agent is administered.
  Advise patients and caregivers:
  - how to treat with an opioid overdose reversal agent in the event of an opioid overdose.
  - to tell family and the people closest to the patient about their opioid overdose reversal agent and to keep it in a place where family and the people closest to the patient can access it in an emergency.
  - to read the Patient Information (or other educational material) that will come with their opioid overdose reversal agent. Emphasize the importance of doing this before an opioid emergency happens, so the patient and caregiver will know what to do.

VIVITROL for All Indications:

- Inform patients on VIVITROL that they may not experience the expected effects from opioid-containing analgesic, antidiarrheal, or antitussive medications.
- Instruct patients that VIVITROL must be prepared and administered by a healthcare provider.
- Advise patients that a reaction at the site of VIVITROL injection may occur. Reactions include pain, tenderness, induration, swelling, erythema, bruising, or pruritus. Serious injection site reactions including necrosis may occur. Some of these injection site reactions have required surgery. Patients should be advised to seek medical attention for worsening skin reactions.
- Advise patients that they should be off all opioids, including opioid-containing medicines, for a minimum of 7 – 10 days before starting VIVITROL in order to avoid precipitation of opioid withdrawal. Patients transitioning from buprenorphine or methadone may be vulnerable to precipitation of withdrawal symptoms for as long as two weeks. Ensure that patients understand that withdrawal precipitated by administration of an opioid antagonist may be severe enough to require hospitalization if they have not been opioid-free for an adequate period of time, and is different from the experience of spontaneous withdrawal that occurs with discontinuation of opioid in a dependent individual. Advise patients that they should not take VIVITROL if they have any symptoms of opioid withdrawal. Advise all patients, including those with alcohol dependence, that it is imperative to notify healthcare providers of any recent use of opioids or any history of opioid dependence before starting VIVITROL to avoid precipitation of opioid withdrawal.
- Advise patients that VIVITROL may cause liver injury. Patients should immediately notify their physician if they develop symptoms and/or signs of liver disease.
- Advise patients that they may experience depression while taking VIVITROL. It is important that patients inform family members and the people closest to the patient that they are taking VIVITROL and that they should call a doctor right away should they become depressed or experience symptoms of depression.
- Advise patients to carry documentation to alert medical personnel to the fact that they are taking VIVITROL (naltrexone for extended-release injectable suspension). This will help to ensure that patients obtain adequate medical treatment in an emergency.
- Advise patients that VIVITROL may cause an allergic pneumonia. Patients should immediately notify their physician if they develop signs and symptoms of pneumonia, including dyspnea, coughing, or wheezing.
- Advise patients that they should not take VIVITROL if they are allergic to VIVITROL or any of the microsphere or diluent components.
- Advise patients that they may experience nausea following the initial injection of VIVITROL. These episodes of nausea tend to be mild and subside within a few days post-injection. Patients are less likely to experience nausea in subsequent injections. Patients should be advised that they may also experience tiredness, headache, vomiting, decreased appetite, painful joints and muscle cramps.
- Advise patients that because VIVITROL is an intramuscular injection and not an implanted device, once VIVITROL is injected, it is not possible to remove it from the body.
- Advise patients that VIVITROL has been shown to treat alcohol and opioid dependence only when used as part of a treatment program that includes counseling and support.
- Advise patients that dizziness may occur with VIVITROL treatment, and they should avoid driving or operating heavy machinery until they have determined how VIVITROL affects them.
- Advise patients to notify their physician if they:
  - become pregnant or intend to become pregnant during treatment with VIVITROL.
  - are breast-feeding.
  - experience respiratory symptoms such as dyspnea, coughing, or wheezing when taking VIVITROL.
  - experience any allergic reactions when taking VIVITROL.
  - experience other unusual or significant side effects while on VIVITROL therapy.

17.1 Frequently Asked Questions About Administering VIVITROL:

1. Can I prepare the suspension prior to my patient's arrival?
  No. You may remove the carton from the refrigerator prior to the patient's arrival, but once the diluent is added to the VIVITROL microspheres, the dose should be mixed and the suspension administered immediately. It is very important to use proper aseptic technique when preparing the suspension [see Dosage and Administration (2.6)].
2. How much time do I have between preparing and administering the dose?
  It is recommended that the suspension be administered immediately once the product has been suspended and transferred into the syringe. If a few minutes' delay occurs after suspension but before transfer into the syringe [see Dosage and Administration (2.6; Figure D)], the vial can be inverted a few times to resuspend and then transferred into the syringe for immediate use [see Dosage and Administration (2.6)].
3. Can I use needles other than those provided in the carton?
  No. The needles in the carton are specially designed for administration of VIVITROL. Do not make any substitutions for components of the carton [see Dosage and Administration (2.6)].
4. The suspension is milky white upon mixing with the diluent. Is this normal?
  Yes. VIVITROL microspheres will form a milky suspension when mixed with the provided diluent [see Dosage and Administration (2.6)].
5. What if a needle clog occurs during administration of the product?
  If a clog occurs during administration, the needle should be withdrawn from the patient, capped with the attached needle protection device, and replaced with the spare administration needle. Gently push on the plunger until a bead of the suspension appears at the tip of the needle. The remainder of the suspension should then be administered into an adjacent site in the same gluteal region [see Dosage and Administration (2.6)].

For additional information, visit www.vivitrol.com or call 1-800-848-4876

Manufactured and marketed by:
Alkermes, Inc.
Waltham, MA 02451

©2025 Alkermes. All rights reserved.
ALKERMES® and VIVITROL® are registered trademarks of Alkermes, Inc.
Printed in U.S.A.
REV: December 2025

US Patent No. 7,919,499

MEDICATION GUIDE

VIVITROL® (viv-i-trol)

(naltrexone for extended-release injectable suspension)

Read this Medication Guide before you start receiving VIVITROL injections and each time you receive an injection. There may be new information. This information does not take the place of talking to your healthcare provider about your medical condition or your treatment.

What is the most important information I should know about VIVITROL?

VIVITROL can cause serious side effects, including:

1. Risk of opioid overdose.
  You can accidentally overdose in two ways.
  - VIVITROL blocks the effects of opioids, such as heroin or opioid pain medicines. Do not take large amounts of opioids, including opioid-containing medicines, such as heroin or prescription pain pills, to try to overcome the opioid-blocking effects of VIVITROL. This can lead to serious injury, coma, or death.
  - After you receive a dose of VIVITROL, its blocking effect slowly decreases and completely goes away over time. If you have used opioid street drugs or opioid-containing medicines in the past, using opioids in amounts that you used before treatment with VIVITROL can lead to overdose and death. You may also be more sensitive to the effects of lower amounts of opioids:
    - after you have gone through detoxification
    - when your next VIVITROL dose is due
    - if you miss a dose of VIVITROL
    - after you stop VIVITROL treatment
    It is important that you tell your family and the people closest to you of this increased sensitivity to opioids and the risk of overdose.
    You or someone close to you should call 911 or get emergency medical help right away if you:
  - have trouble breathing
  - become very drowsy with slowed breathing
  - have slow, shallow breathing (little chest movement with breathing)
  - feel faint, very dizzy, confused, or have unusual symptoms
  Ask your healthcare provider about medicines like naloxone or nalmefene that can be used in an emergency to reverse an opioid overdose. You must call 911 or get emergency medical help right away to treat an opioid overdose or accidental use of an opioid, even if naloxone or nalmefene is administered.
2. Severe reactions at the site of the injection (injection site reactions). Some people on VIVITROL have had severe injection site reactions, including tissue death (necrosis). Some of these injection site reactions have required surgery. VIVITROL must be injected by a healthcare provider. Call your healthcare provider right away if you notice any of the following at any of your injection sites:
  - intense pain
  - the area feels hard
  - large area of swelling
  - lumps
  - blisters
  - an open wound
  - a dark scab
  Tell your healthcare provider about any reaction at an injection site that concerns you, gets worse over time, or does not get better by two weeks after the injection.
3. Sudden opioid withdrawal.
  Anyone who receives a VIVITROL injection must not use any type of opioid (must be opioid-free) including street drugs, prescription pain medicines, cough, cold, or diarrhea medicines that contain opioids, or opioid dependence treatments, buprenorphine or methadone, for at least 7 to 14 days before starting VIVITROL. Using opioids in the 7 to 14 days before you start receiving VIVITROL may cause you to suddenly have symptoms of opioid withdrawal when you get the VIVITROL injection. Sudden opioid withdrawal can be severe, and you may need to go to the hospital.
  You must be opioid-free before receiving VIVITROL unless your healthcare provider decides that you don't need to go through detox first. Instead, your doctor may decide to give your VIVITROL injection in a medical facility that can treat you for sudden opioid withdrawal.
4. Liver damage or hepatitis. Naltrexone, the active ingredient in VIVITROL, can cause liver damage or hepatitis.
  Tell your healthcare provider if you have any of the following symptoms of liver problems during treatment with VIVITROL:
  - stomach area pain lasting more than a few days
  - dark urine
  - yellowing of the whites of your eyes
  - tiredness

Your healthcare provider may need to stop treating you with VIVITROL if you get signs or symptoms of a serious liver problem.

What is VIVITROL?

VIVITROL is a prescription injectable medicine used to:

- treat alcohol dependence. You should stop drinking before starting VIVITROL.
- prevent relapse to opioid dependence, after opioid detoxification.
  This means that if you take opioids or opioid-containing medicines, you must stop taking them before you start receiving VIVITROL. See “What is the most important information I should know about VIVITROL?”

To be effective, treatment with VIVITROL must be used with other alcohol or drug recovery programs such as counseling. VIVITROL may not work for everyone.

It is not known if VIVITROL is safe and effective in children.

Who should not receive VIVITROL?

Do not receive VIVITROL if you:

- are using or have a physical dependence on opioid-containing medicines or opioid street drugs. See “What is the most important information I should know about VIVITROL?”
  To see whether you have a physical dependence on opioid-containing medicines or opioid street drugs, your healthcare provider may give you a small injection of a medicine called naloxone. This is called a naloxone challenge test. If you get symptoms of opioid withdrawal after the naloxone challenge test, do not start treatment with VIVITROL at that time. Your healthcare provider may repeat the test after you have stopped using opioids to see whether it is safe to start VIVITROL.
- are having opioid withdrawal symptoms. Opioid withdrawal symptoms may happen when you have been taking opioid-containing medicines or opioid street drugs regularly and then stop.
  Symptoms of opioid withdrawal may include: anxiety, sleeplessness, yawning, fever, sweating, teary eyes, runny nose, goose bumps, shakiness, hot or cold flushes, muscle aches, muscle twitches, restlessness, nausea and vomiting, diarrhea, or stomach cramps. See “What is the most important information I should know about VIVITROL?” Tell your healthcare provider if you have any of these symptoms before taking VIVITROL.
- are allergic to naltrexone or any of the ingredients in VIVITROL or the liquid used to mix VIVITROL (diluent). See the end of this Medication Guide for a complete list of ingredients in VIVITROL and the diluent.

What should I tell my healthcare provider before receiving VIVITROL?

Before you receive VIVITROL, tell your healthcare provider if you:

- have liver problems
- use or abuse street (illegal) drugs
- have hemophilia or other bleeding problems
- have kidney problems
- have any other medical conditions
- are pregnant or plan to become pregnant. It is not known if VIVITROL will harm your unborn baby.
- are breastfeeding. It is not known if VIVITROL passes into your milk, and if it can harm your baby. Naltrexone, the active ingredient in VIVITROL, is the same active ingredient in tablets taken by mouth that contain naltrexone. Naltrexone from tablets passes into breast milk. Talk to your healthcare provider about whether you will breastfeed or take VIVITROL. You should not do both.

Tell your healthcare provider about all the medicines you take, including prescription and non-prescription medicines, vitamins, and herbal supplements.

Especially tell your healthcare provider if you take any opioid-containing medicines for pain, cough or colds, or diarrhea. See “What is the most important information I should know about VIVITROL?”

If you are being treated for alcohol dependence but also use or are addicted to opioid-containing medicines or opioid street drugs, it is important that you tell your healthcare provider before starting VIVITROL to avoid having sudden opioid withdrawal symptoms when you start VIVITROL treatment.

Know the medicines you take. Keep a list of them to show your healthcare provider and pharmacist when you get a new medicine.

How will I receive VIVITROL?

- VIVITROL is injected by a healthcare provider, about 1 time each month.
- VIVITROL must be injected by a healthcare provider. Do not attempt to inject yourself with VIVITROL. Serious reactions, some that may require hospitalization, might happen.
- VIVITROL is given as an injection into a muscle in your buttocks using a special needle that comes with VIVITROL.
- After VIVITROL is injected, it lasts for a month and it cannot be removed from the body.
- If you miss your appointment for your VIVITROL injection, schedule another appointment as soon as possible. See “What is the most important information I should know about VIVITROL?”
- Whenever you need medical treatment, be sure to tell the treating healthcare provider that you are receiving VIVITROL injections and mention when you got your last dose. This is important because VIVITROL can also block the effects of opioid-containing medicines that might be prescribed for you for pain, cough or colds, or diarrhea.
- Carry written information with you at all times to alert healthcare providers that you are taking VIVITROL, so that they can treat you properly in an emergency. Ask your healthcare provider how you can get a wallet card to carry with you.

What should I avoid while receiving VIVITROL?

Do not drive a car, operate machinery, or do other dangerous activities until you know how VIVITROL affects you. VIVITROL may make you feel dizzy and sleepy. See “What are the possible side effects of VIVITROL?”

What are the possible side effects of VIVITROL?

VIVITROL can cause serious side effects, including:

- See “What is the most important information I should know about VIVITROL?”
- Depressed mood. Sometimes this leads to suicide, or suicidal thoughts, and suicidal behavior. Tell your family members and people closest to you that you are taking VIVITROL.
  You, a family member, or the people closest to you should call your healthcare provider right away if you become depressed or have any of the following symptoms of depression, especially if they are new, worse, or worry you:
  - You feel sad or have crying spells.
  - You are no longer interested in seeing your friends or doing things you used to enjoy.
  - You are sleeping a lot more or a lot less than usual.
  - You feel hopeless or helpless.
  - You are more irritable, angry, or aggressive than usual.
  - You are more or less hungry than usual or notice a big change in your body weight.
  - You have trouble paying attention.
  - You feel tired or sleepy all the time.
  - You have thoughts about hurting yourself or ending your life.
- Pneumonia. Some people receiving VIVITROL treatment have had a certain type of pneumonia that is caused by an allergic reaction. If this happens to you, you may need to be treated in the hospital. Tell your healthcare provider right away if you have any of these symptoms during treatment with VIVITROL:
  - shortness of breath or wheezing
  - coughing that does not go away
- Serious allergic reactions. Serious allergic reactions can happen during or soon after an injection of VIVITROL. Tell your healthcare provider or get medical help right away if you have any of these symptoms of a serious allergic reaction.
  - skin rash
  - swelling of your face, eyes, mouth, or tongue
  - trouble breathing or wheezing
  - chest pain
  - feeling dizzy or faint

Common side effects of VIVITROL may include:

- nausea. Nausea may happen after your first VIVITROL injection and usually improves within a few days. Nausea is less likely with future injections of VIVITROL.
- sleepiness
- headache
- dizziness
- vomiting
- decreased appetite
- painful joints
- muscle cramps
- cold symptoms
- trouble sleeping
- toothache

Tell your healthcare provider if you have any side effect that bothers you or that does not go away.

These are not all the side effects of VIVITROL. For more information, ask your healthcare provider or pharmacist.

Call your doctor for medical advice about side effects. You may report side effects to FDA at 1-800-FDA-1088.

General information about VIVITROL

Medicines are sometimes prescribed for purposes other than those listed in a Medication Guide. This Medication Guide summarizes the most important information about VIVITROL. If you would like more information, talk with your healthcare provider. You can ask your healthcare provider or pharmacist for information about VIVITROL that is written for health professionals.

For more information about VIVITROL call 1-800-848-4876, Option #1 or go to www.vivitrol.com.

What are the ingredients in VIVITROL?

Active ingredient: naltrexone

Inactive ingredients: polylactide-co-glycolide (PLG)

Diluent ingredients: carboxymethylcellulose sodium, polysorbate 20, sodium chloride, sodium hydroxide and hydrochloric acid as pH adjusters, in water for injection.

This Medication Guide has been approved by the U.S. Food and Drug Administration.

Manufactured and marketed by:

Alkermes, Inc.
Waltham, MA 02451

Revised: December 2025

Alkermes® and VIVITROL® are registered trademarks of Alkermes, Inc.

PACKAGE LABEL

PACKAGE LABEL- PRINCIPAL DISPLAY PANEL-VIVITROL® COMMERCIAL KIT CARTON

NDC: 65757-300-01

Rx Only

VIVITROL®

(naltrexone for extended-release injectable suspension)

380 mg/vial

VIVITROL must be injected by a healthcare provider. For gluteal intramuscular injection only.

Severe injection site reactions that required surgery and/or hospitalization have occurred with VIVITROL.

Healthcare provider: Dispense the enclosed Medication Guide to each patient

Please see accompanying full prescribing information.

Dispense the enclosed Medication Guide to each patient.

Must reconstitute VIVITROL Microspheres with enclosed diluent prior to administration. Upon reconstitution with 3.4 mL diluent, each mL will contain 95 mg of naltrexone.

Each Carton Contains:

1) One vial of 380 mg of VIVITROL (naltrexone for extended-release injectable suspension)*

2) One vial containing 4 mL of diluent†

3) One 5-mL prepackaged syringe

4) One 20-gauge 1-inch needle

5) Two 20-gauge 1½-inch safety needles

6) Two 20-gauge 2-Inch safety needles

*VIVITROL Microspheres: 380 mg of naltrexone per vial, contained in a biodegradable matrix of 75:25 polylactide-co-glycolide at a concentration of 337 mg of naltrexone per gram of microspheres.

†Each mL of diluent contains 30.0 mg of carboxymethylcellulose sodium, 1.0 mg of polysorbate 20, 9.0 mg of sodium chloride, and sodium hydroxide and hydrochloric acid as pH adjusters, in water for injection.

Storage:

Store in outer carton, refrigerated at 2°C to 8°C (36°F to 46°F).

If refrigeration is unavailable, product can be stored at temperatures not exceeding 25 °C (77 °F) for no more than 7 days prior to administration. Do not expose unrefrigerated product to temperatures above 25 °C (77 °F). Do not freeze.

Remove the carton from the refrigerator and allow it to come to room temperature prior to preparation.

Keep out of reach of children.

ALKERMES® and VIVITROL® are registered trademarks of Alkermes, Inc. Manufactured and marketed by Alkermes, Inc. www.vivitrol.com 1-800-848-4876

Alkermes®

PACKAGE LABEL

PACKAGE LABEL- PRINCIPAL DISPLAY PANEL-VIVITROL ®MICROSPHERES VIAL LABEL

NDC: 65757-302-02

Rx Only

VIVITROL® Microspheres, 380 mg/vial

(naltrexone for extended-release injectable suspension)

FOR GLUTEAL INTRAMUSCULAR INJECTION ONLY. Must be reconstituted with the enclosed diluent prior to administration. Upon reconstitution with 3.4 mL diluent, each mL will contain 95 mg naltrexone. See Package Insert for dose preparation and administration. Single-dose Vial. Discard unused portion. Storage: Refrigerate at 2°C to 8°C (36°F to 46°F). Manufactured and marketed by: Alkermes, Inc., Waltham, MA 02451

PACKAGE LABEL

PACKAGE LABEL- PRINCIPAL DISPLAY PANEL-VIVITROL® DILUENT VIAL LABEL

NDC: 65757-304-03

Rx Only

Diluent for use only with
VIVITROL® microspheres, 4 mL/Vial

Each mL of diluent contains 30.0 mg of carboxymethylcellulose sodium, 1.0 mg of polysorbate 20, 9.0 mg of sodium chloride, and sodium hydroxide and hydrochloric acid as pH adjusters, in water for injection. Single-dose Vial. Discard unused portion. Not for direct administration. See Package Insert for dose preparation. Storage: Refrigerate at 2°C to 8°C (36°F to 46°F). 4 mL (to withdraw 3.4 mL for reconstitution).

Manufactured for: Alkermes, Inc., Waltham, MA 02451

PACKAGE LABEL

PACKAGE LABEL- PRINCIPAL DISPLAY PANEL-VIVITROL® SAMPLE KIT CARTON

SAMPLE – NOT FOR RESALE

NDC: 65757-301-01

Rx Only

VIVITROL®

(naltrexone for extended-release injectable suspension)

380 mg/vial

VIVITROL must be injected by a healthcare provider. For gluteal intramuscular injection only.

Severe injection site reactions that required surgery and/or hospitalization have occurred with VIVITROL.

Healthcare provider: Dispense the enclosed Medication Guide to each patient

Please see accompanying full prescribing information.

Dispense the enclosed Medication Guide to each patient.

PACKAGE LABEL

PACKAGE LABEL- PRINCIPAL DISPLAY PANEL- SAMPLE VIVITROL® MICROSPHERES VIAL LABEL

NDC: 65757-303-02

Rx Only

Vivitrol® microspheres, 380 mg/vial

(naltrexone for extended-release injectable suspension)

SAMPLE – NOT FOR SALE

FOR GLUTEAL INTRAMUSCULAR INJECTION ONLY. Must be reconstituted with
the enclosed diluent prior to administration. Upon reconstitution with 3.4 mL
diluent, each mL will contain 95 mg naltrexone. See Package Insert for dose
preparation and administration. Single-dose Vial. Discard unused portion.

Storage: Refrigerate at 2°C to 8°C (36°F to 46°F).

PACKAGE LABEL

PACKAGE LABEL- PRINCIPAL DISPLAY PANEL- SAMPLE VIVITROL® DILUENT VIAL LABEL

NDC: 65757-305-03

Rx Only

Diluent for use only with VIVITROL®
microspheres, 4 mL/vial

SAMPLE - NOT FOR SALE

Each mL of diluent contains 30.0 mg of carboxymethylcellulose sodium,
1.0 mg of polysorbate 20, 9.0 mg of sodium chloride, and sodium
hydroxide and hydrochloric acid as pH adjusters, in water for injection.

Single-dose Vial. Discard unused portion. Not for direct
administration. Storage: Refrigerate at 2°C to 8°C (36°F to 46°F).

4 mL (to withdraw 3.4 mL for reconstitution).